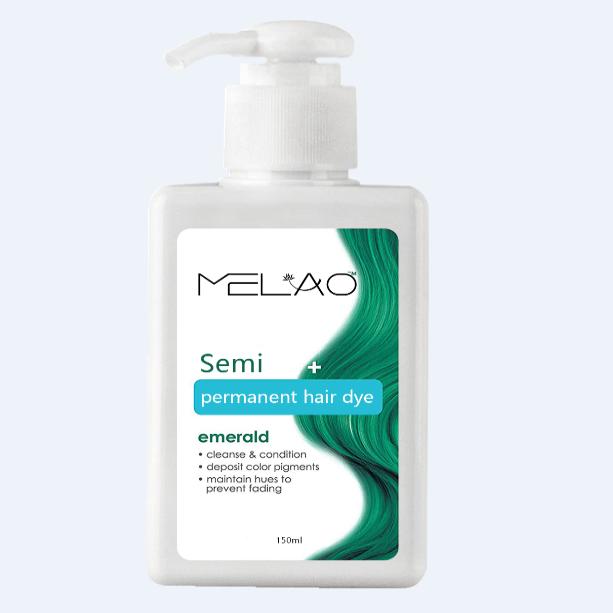 DRUG LABEL: MELAO Hair Color Depositing Conditioner
NDC: 83566-590 | Form: CREAM
Manufacturer: Guangzhou Yilong Cosmetics Co., Ltd
Category: otc | Type: HUMAN OTC DRUG LABEL
Date: 20240827

ACTIVE INGREDIENTS: CUPRIC TRIETHANOLAMINE 1 g/100 g
INACTIVE INGREDIENTS: GLYCERIN; ((R)-BINAP RUCL BENZENE)CL; WATER O-15; CARBOMER 1342; ETHYLENE-VINYL ACETATE COPOLYMER (19% VINYLACETATE); PROPYLENE GLYCOL DICAPRYLATE/DICAPRATE; DMDM HYDANTOIN

MELAO Hair Color Depositing Conditioner

Active ingredients

Triethanolamine 1%

Inactive ingredients

Water 78%

Carbomer 10%

DMDM Hydantoin 5%

Ethylene/Acrylic Acid/VA Copolymer 4%

Propylene Glycol 0.5%

Glycerin 0.5%

Cl 15985 0.5%

Fragrance 0.5%

Purpose

Moisture

Uses

Step 1: Clean and thoroughly dry your hair.

Step 2: Rotate the bottle cap to open the product.

Step 3: Gently apply to the surface of the hair.

Warning

For external use only.

Stop use and ask a doctor if

rash occurs.

.Do not use

on damaged or broken skin.

When using this product

keep out of eyes. Rinse withwater to remove.

Keep out of reach of children.

If swallowed, get medical help or contact a Poison Control Center right away.

DOSAGE & ADMINISTRATION

Squeeze out an appropriate amount of product and spread evenly on skin.